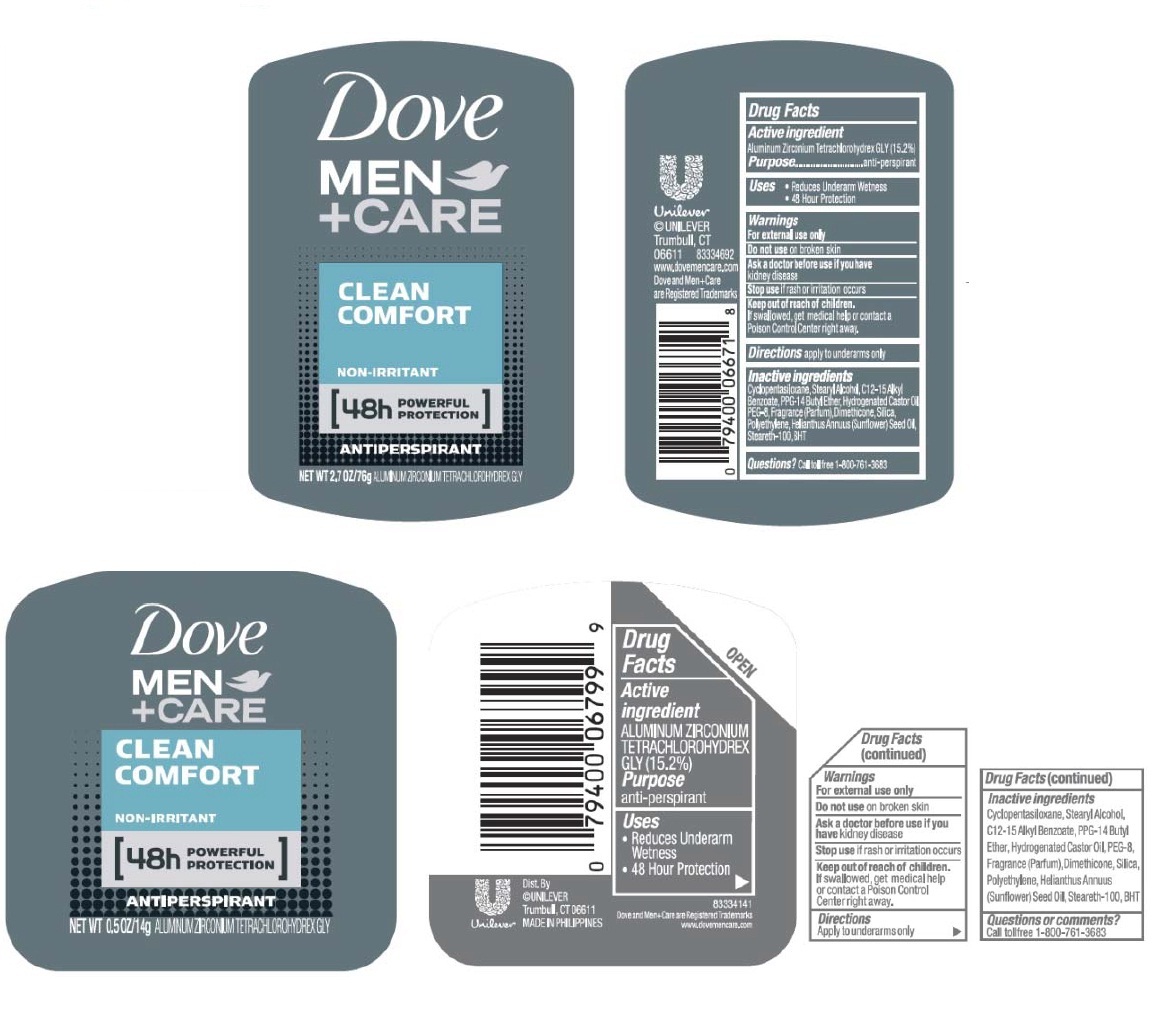 DRUG LABEL: Dove Men plus Care
NDC: 64942-1819 | Form: STICK
Manufacturer: Conopco, Inc. d/b/a Unilever
Category: otc | Type: HUMAN OTC DRUG LABEL
Date: 20241108

ACTIVE INGREDIENTS: ALUMINUM ZIRCONIUM TETRACHLOROHYDREX GLY 15.2 g/100 g
INACTIVE INGREDIENTS: CYCLOMETHICONE 5; STEARYL ALCOHOL; ALKYL (C12-15) BENZOATE; PPG-14 BUTYL ETHER; HYDROGENATED CASTOR OIL; POLYETHYLENE GLYCOL 400; DIMETHICONE; SILICON DIOXIDE; HIGH DENSITY POLYETHYLENE; SUNFLOWER OIL; STEARETH-100; BUTYLATED HYDROXYTOLUENE

Dove Men plus Care Clean Comfort Antiperspirant

Active Ingredient

Aluminum Zirconium Tetrachlorohydrex GLY (15.2%)

Purpose
anti-perspirant

Uses

· Reduces underarm wetness

· 48 hour protection

Warnings
For External Use Only

Do not use on broken skin

Ask a doctor before use if you have kidney disease

Stop use if rash or irritation occurs

Keep out of reach of children. If swallowed, get medical help or contact a Poison Control Center right away

Directions
Apply to underarms only

Inactive ingredients
Cyclopentasiloxane, Stearyl Alcohol, C12-15 Alkyl Benzoate, PPG-14 Butyl Ether, Hydrogenated Castor Oil, PEF-8, Fragrance (Parfum), Dimethicone, Polyethylene, Helianthus Annuus (Sunflower) Seed Oil, Steareth-100, BHT.

Questions or comments? Call toll free 1-800-761-3683